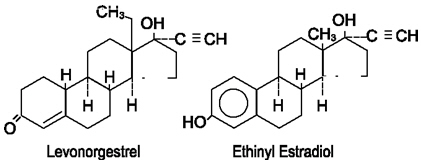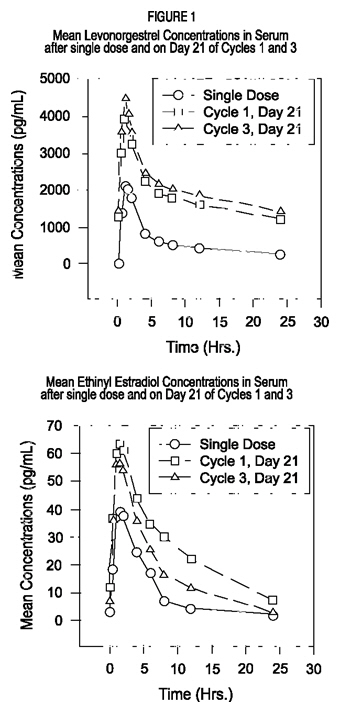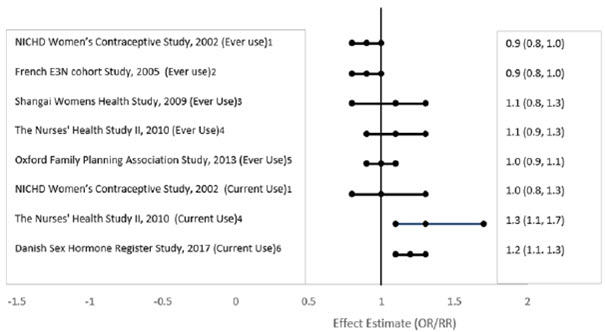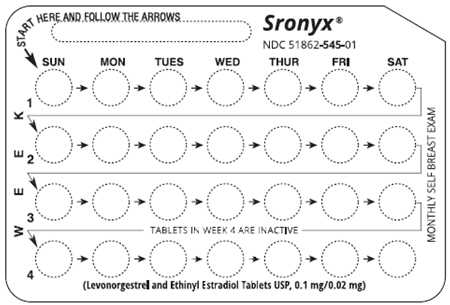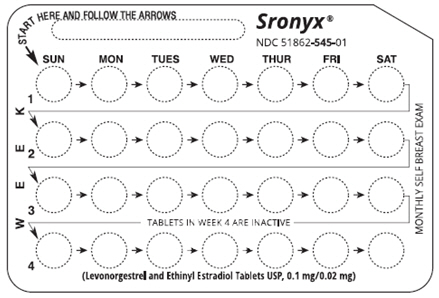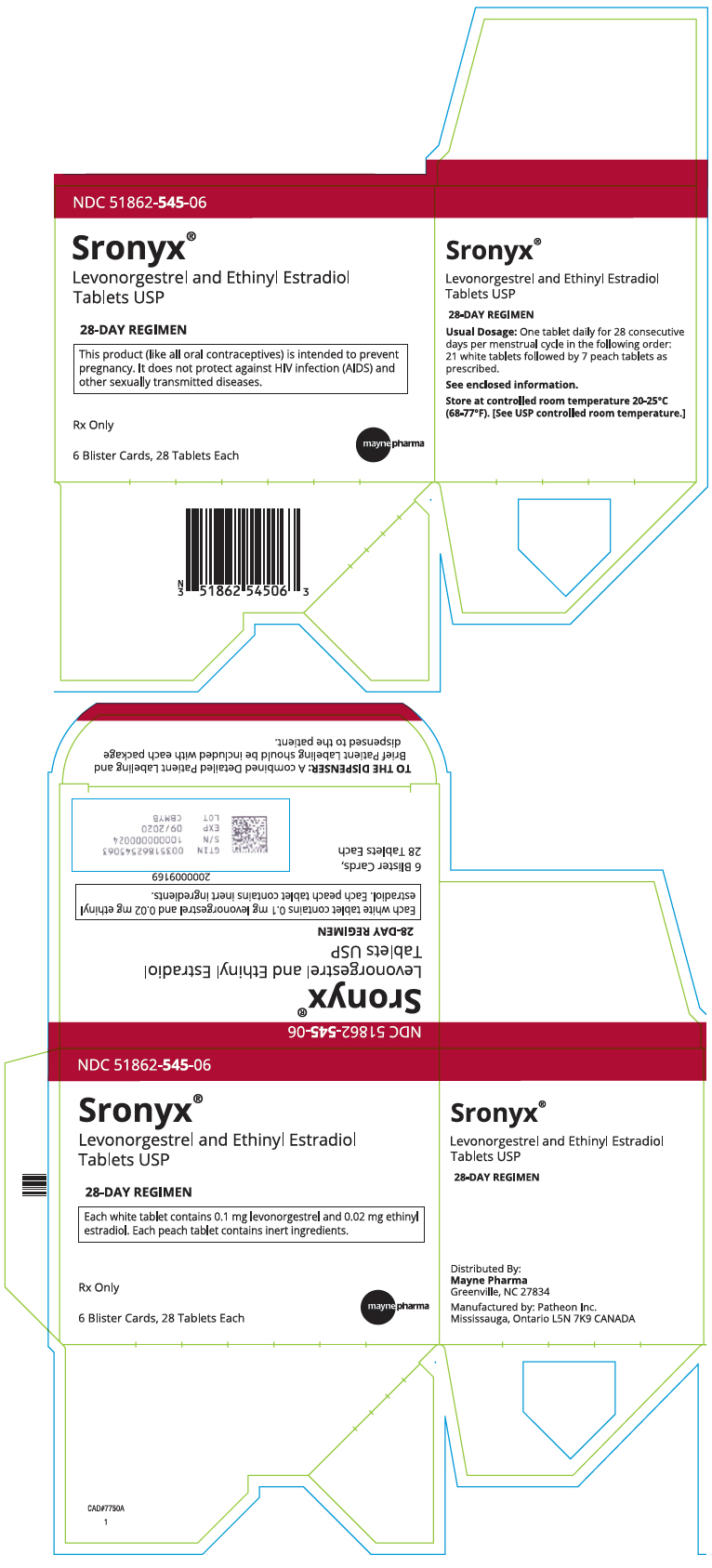 DRUG LABEL: SRONYX
NDC: 51862-545 | Form: KIT | Route: ORAL
Manufacturer: Mayne Pharma Inc.
Category: prescription | Type: HUMAN PRESCRIPTION DRUG LABEL
Date: 20250724

ACTIVE INGREDIENTS: LEVONORGESTREL 0.1 mg/1 1; ETHINYL ESTRADIOL 0.02 mg/1 1
INACTIVE INGREDIENTS: CROSCARMELLOSE SODIUM; LACTOSE MONOHYDRATE; MAGNESIUM STEARATE; POVIDONE, UNSPECIFIED; MICROCRYSTALLINE CELLULOSE; FD&C YELLOW NO. 6; ANHYDROUS LACTOSE; MAGNESIUM STEARATE; MICROCRYSTALLINE CELLULOSE; LACTOSE MONOHYDRATE

SRONYX®
(Levonorgestrel and Ethinyl Estradiol Tablets USP)

PHYSICIAN LABELING

Rx only

Patients should be counseled that this product does not protect against HIV infection (AIDS) and other sexually transmitted diseases.

DESCRIPTION

Each cycle of Sronyx®(Levonorgestrel and Ethinyl Estradiol Tablets USP) consists of 21 white active tablets each containing 0.1 mg levonorgestrel and 0.02 mg ethinyl estradiol; and seven peach tablets – inert. The inactive ingredients are Croscarmellose Sodium NF, Lactose Monohydrate NF, Magnesium Stearate NF, Microcrystalline Cellulose (PH 102) NF, and Povidone (K29/32) NF. Each inactive, placebo tablet contains the following inactive ingredients: FD & C Yellow #6 Lake 35-42%, Lactose Anhydrous (DT Micro) NF, Lactose Monohydrate (200M) NF, Magnesium Stearate NF and Microcrystalline Cellulose NF.

Levonorgestrel has a molecular weight of 312.4 and a molecular formula of C21H28O2. Ethinyl estradiol has a molecular weight of 296.4 and a molecular formula of C20H24O2. The structural formulas are as follows:

CLINICAL PHARMACOLOGY

Combination oral contraceptives act by suppression of gonadotropins. Although the primary mechanism of this action is inhibition of ovulation, other alterations include changes in the cervical mucus (which increase the difficulty of sperm entry into the uterus) and the endometrium (which reduce the likelihood of implantation).

PHARMACOKINETICS

Absorption

No specific investigation of the absolute bioavailability of levonorgestrel and ethinyl estradiol of Levonorgestrel and Ethinyl Estradiol Tablets USP in humans has been conducted. However, literature indicates that levonorgestrel is rapidly and completely absorbed after oral administration and is not subject to first-pass metabolism. Ethinyl estradiol is rapidly and almost completely absorbed from the gastrointestinal tract but, due to first-pass metabolism in gut mucosa and liver, the absolute bioavailability of ethinyl estradiol is about 40%.

After a single dose of three Levonorgestrel and Ethinyl Estradiol Tablets USP to 17 women under fasting conditions, the extents of absorption of levonorgestrel and ethinyl estradiol were 98.6% and 99.0%, respectively, relative to the same dose of the 2 drugs when given as a microcrystalline suspension in water. The effect of food on the bioavailability of Levonorgestrel and Ethinyl Estradiol Tablets USP following oral administration has not been evaluated.

The pharmacokinetics of levonorgestrel and ethinyl estradiol following daily administration of Levonorgestrel and Ethinyl Estradiol Tablets USP for 21 days per cycle for three cycles, were determined in 18 women. Estimates of the pharmacokinetic parameters of levonorgestrel and ethinyl estradiol following single and multiple dose administration of Levonorgestrel and Ethinyl Estradiol Tablets USP are summarized in Table I. Mean levonorgestrel and ethinyl estradiol levels after a single dose and on day 21 at steady state are shown in Figure 1.

The pharmacokinetics of total levonorgestrel are non-linear due to an increase in binding to SHBG, which is attributed to increased SHBG levels that are induced by the daily administration of ethinyl estradiol. Increased binding of levonorgestrel to SHBG leads to decreased clearance of levonorgestrel. Observed maximum levonorgestrel concentrations increased from day 1 to day 21 of the 1st and 3rd cycles by 66% and 83%, respectively.

In calculating the mean concentration for ethinyl estradiol, any individual subject value below the quantifiable limit (i.e., 20 pg/mL) was converted to 0; and the 0 values were included for calculation of the mean concentration.

Table I provides a summary of Levonorgestrel and Ethinyl Estradiol pharmacokinetic parameters.

TABLE I MEAN (SD) PHARMACOKINETIC PARAMETERS OF LEVONORGESTREL AND ETHINYL ESTRADIOL TABLETS USP AFTER SINGLE DOSE AND AFTER MULTIPLE DOSING FOR 3 CYCLES
Levonorgestrel
Day (cycle) | Cmax ng/mL | tmax h | AUC ng∙h/mL |  | CL/F mL/min/kg | Vz L | SHBG nmol/L
1 | 2.36 (0.79) | 1.3 (0.4) | 29.2 (10.0) |  | 1.0 (0.3) | 129 (46) | 64.5 (22.0)
 |  |  | AUC (0-24h) ng∙h/mL
21 (1) | 4.04 (2.08) | 1.0 (0.3) | 43.8 (22.4) |  | 0.73 (0.34) | 106 (42) | 94.7 (37.4)
21 (3) | 4.53 (1.94) | 1.0 (0.3) | 49.5 (24.5) |  | 0.65 (0.33) | 96 (35) | 107.4 (45.8)
Ethinyl Estradiol
Day (cycle) |  | Cmax pg/mL |  | tmax h |  | AUC (0-24) pg∙h/mL
1 |  | 49.5 (13.4) |  | 1.5 (0.4) |  | 298 (215)
21(1) |  | 66.2 (29.5) |  | 1.4 (0.4) |  | 596 (494)
21(3) |  | 58.1 (19.3) |  | 1.4 (0.3) |  | 417 (289)
Cmax= maximum concentration
tmax= time to maximum concentration
AUC = area under the drug concentration curve from time 0 to infinity
CL/f = oral clearance
Vz = volume of distribution
SHBG = sex hormone-binding globulin
AUC (0-24) = area under the drug concentration time curve from time 0 to 24 hours; this represents the area for one dosing interval at steady state.

Distribution

Levonorgestrel in serum is primarily bound to SHBG. Protein binding values for levonorgestrel are provided in Table II. Ethinyl estradiol is about 97% bound to plasma albumin. Ethinyl estradiol does not bind to SHBG, but induces SHBG synthesis.

TABLE II. Protein binding (mean ± SD) of levonorgestrel in pools of serum samples collected from 18 women after a single dose of Levonorgestrel and Ethinyl Estradiol Tablets USP and following administration (once daily) over 3×21 days.
Parameter | Single Dose |  | Cycle 2 |  | Cycle 4
% free | 1.11 | (0.27) | 0.79 | (0.22) | 0.80 | (0.23)
% SHBG-bound | 64.5 | (8.54) | 75.6 | (6.59) | 74.7 | (7.89)
% albumin-bound | 34.4 | (8.28) | 23.6 | (6.41) | 24.5 | (7.67)

Metabolism

Levonorgestrel

The most important metabolic pathway occurs in the reduction of the Δ4-3-oxo group and hydroxylation at positions 2α, 1ß, and 16ß, followed by conjugation. Most of the metabolites that circulate in the blood are sulfates of 3α, 5ß-tetrahydro-levonorgestrel, while excretion occurs predominantly in the form of glucuronides. Some of the parent levonorgestrel also circulates as 17ß-sulfate. Metabolic clearance rates may differ among individuals by several-fold, and this may account in part for the wide variation in levonorgestrel concentrations among users.

Ethinyl estradiol

Cytochrome P450 enzymes (CYP3A4) in the liver are responsible for the 2- hydroxylation that is the major oxidative reaction. The 2-hydroxy metabolite is further transformed by methylation and glucuronidation prior to urinary and fecal excretion. Levels of Cytochrome P450 (CYP3A) vary widely among individuals and can explain the variation in the rates of ethinyl estradiol 2-hydroxylation. Ethinyl estradiol is excreted in the urine and feces as glucuronide and sulfate conjugates and undergoes enterohepatic circulation.

Excretion

The elimination half-life for levonorgestrel after a single dose of Levonorgestrel and Ethinyl Estradiol Tablets USP is 25.4 ± 9.7 hours. Levonorgestrel and its metabolites are primarily excreted in the urine. The elimination half-life of ethinyl estradiol has been reported to be between 15 and 25 hours.

SPECIAL POPULATIONS

Hepatic Insufficiency

No formal studies have evaluated the effect of hepatic disease on the disposition of Levonorgestrel and Ethinyl Estradiol Tablets USP. However, steroid hormones may be poorly metabolized in patients with impaired liver function.

Renal Insufficiency

No formal studies have evaluated the effect of renal disease on the disposition of Levonorgestrel and Ethinyl Estradiol Tablets USP.

Drug-Drug Interactions

Interactions between ethinyl estradiol and other drugs have been reported in the literature.

• Interactions with Absorption

Diarrhea may increase gastrointestinal motility and reduce hormone absorption. Similarly, any drug which reduces gut transit time may reduce hormone concentrations in the blood.

• Interactions with Metabolism

Gastrointestinal Wall

Sulfation of ethinyl estradiol has been shown to occur in the gastrointestinal wall. Therefore, drugs which act as competitive inhibitors for sulfation in the gastrointestinal wall may increase ethinyl estradiol bioavailability.

Hepatic metabolism

Interactions can occur with drugs that induce microsomal enzymes which can decrease ethinyl estradiol concentrations (e.g., rifampin, barbiturates, phenylbutazone, phenytoin, griseofulvin).

• Interference with Enterohepatic Circulation

Some clinical reports suggest that enteroheptic circulation of estrogens may decrease when certain antibiotic agents are given, which may reduce ethinyl estradiol concentrations (e.g., ampicillin, tetracycline).

• Interference in the Metabolism of Other Drugs

Ethinyl estradiol may interfere with the metabolism of other drugs by inhibiting hepatic microsomal enzymes or by inducing hepatic drug conjugation, particularly glucuronidation. Accordingly, plasma and tissue concentrations may either be increased or decreased, respectively (e.g., cyclosporin, theophylline).

INDICATIONS AND USAGE

Oral contraceptives are indicated for the prevention of pregnancy in women who elect to use this product as a method of contraception.

Oral contraceptives are highly effective. Table III lists the typical accidental pregnancy rates for users of combination oral contraceptives and other methods of contraception. The efficacy of these contraceptive methods, except sterilization, depends upon the reliability with which they are used. Correct and consistent use of methods can result in lower failure rates.

Table III Percentage of women experiencing an unintended pregnancy during the first year of typical use and first year of perfect use of contraception and the percentage continuing use at the end of the first year. United States.
 | % of Women Experiencing an Accidental Pregnancy within the First Year of Use |  | % of Women Continuing Use at One Year [Among couples attempting to avoid pregnancy, the percentage who continue to use a method for one year.]
Method (1) | Typical Use [Among typical couples who initiate use of a method (not necessarily for the first time), the percentage who experience an accidental pregnancy during the first year if they do not stop use for any other reason.] (2) | Perfect Use [Among couples who initiate use of a method (not necessarily for the first time) and who use it perfectly (both consistently and correctly), the percentage who experience an accidental pregnancy during the first year if they do not stop use for any other reason.] (3) | (4)
Chance | 85 | 85
Spermicides [Foams, creams, gels, vaginal suppositories, vaginal film.] | 26 | 6 | 40
Periodic abstinence | 25 |  | 63
Calendar |  | 9
Ovulation method |  | 3
Sympto-thermal [Cervical mucus (ovulation) method supplemented by calendar in the pre-ovulatory and basal body temperature in the post-ovulatory phases.] |  | 2
Post Ovulation |  | 1
Withdrawal | 19 | 4
Cap [With spermicidal cream or jelly.]
Parous women | 40 | 26 | 42
Nulliparous women | 20 | 9 | 56
Sponge
Parous women | 40 | 20 | 42
Nulliparous women | 20 | 9 | 56
Diaphragm | 20 | 6 | 56
Condom [Without spermicides.]
Female (Reality) | 21 | 5 | 56
Male | 14 | 3 | 61
Pill | 5 |  | 71
Progestin only |  | 0.5
Combined |  | 0.1
IUD
Progesterone T | 2 | 1.5 | 81
Copper T380A | 0.8 | 0.6 | 78
Lng 20 | 0.1 | 0.1 | 81
Depo Provera | 0.3 | 0.3 | 70
Norplant and Norplant-2 | 0.05 | 0.05 | 88
Female sterilization | 0.5 | 0.5 | 100
Male sterilization | 0.15 | 0.10 | 100
Source: Trussell J, Contraceptive efficacy. In Hatcher RA, Trussell J, Stewart F, Cates W, Stewart GK, Kowal D, Guest F, Contraceptive Technology: Seventeenth Revised Edition.New York NY: Irvington Publishers, 1998.
4 The percentages becoming pregnant in columns (2) and (3) are based on data from populations where contraception is not used and from women who cease using contraception in order to become pregnant. Among such populations, about 89% become pregnant within one year. This estimate was lowered slightly (to 85%) to represent the percentage who would become pregnant within one year among women now relying on reversible methods of contraception if they abandoned contraception altogether.

CONTRAINDICATIONS

Levonorgestrel and ethinyl estradiol tablets are contraindicated in females who are known to have or develop the following conditions:

- Thrombophlebitis or thromboembolic disorders
- A past history of deep-vein thrombophlebitis or thromboembolic disorders
- Cerebral-vascular or coronary-artery disease
- Current diagnosis of, or history of, breast cancer, which may be hormone sensitive
- Carcinoma of the endometrium or other known or suspected estrogen dependent neoplasia
- Undiagnosed abnormal genital bleeding
- Cholestatic jaundice of pregnancy or jaundice with prior pill use
- Hepatic adenomas or carcinomas
- Known or suspected pregnancy
- Are receiving Hepatitis C drug combinations containing ombitasvir/paritaprevir/ritonavir, with or without dasabuvir, due to the potential for ALT elevations (see Warnings, RISK OF LIVER ENZYME ELEVATIONS WITH CONCOMITANT HEPATITIS C TREATMENT).

WARNINGS

BOXED WARNING

Cigarette smoking increases the risk of serious cardiovascular side effects from oral contraceptive use. This risk increases with age and with heavy smoking (15 or more cigarettes per day) and is quite marked in women over 35 years of age. Women who use oral contraceptives should be strongly advised not to smoke.

The use of oral contraceptives is associated with increased risks of several serious conditions including myocardial infarction, thromboembolism, stroke, hepatic neoplasia, gallbladder disease, and hypertension, although the risk of serious morbidity or mortality is very small in healthy women without underlying risk factors. The risk of morbidity and mortality increases significantly in the presence of other underlying risk factors such as hypertension, hyperlipidemias, obesity and diabetes.

Practitioners prescribing oral contraceptives should be familiar with the following information relating to these risks.

The information contained in this package insert is based principally on studies carried out in patients who used oral contraceptives with higher formulations of estrogens and progestogens than those in common use today. The effect of long-term use of the oral contraceptives with lower formulations of both estrogens and progestogens remains to be determined.

Throughout this labeling, epidemiologic studies reported are of two types: retrospective or case control studies and prospective or cohort studies. Case control studies provide a measure of the relative risk of a disease, namely, a ratio of the incidence of a disease among oral contraceptive users to that among nonusers. The relative risk does not provide information on the actual clinical occurrence of a disease. Cohort studies provide a measure of attributable risk, which is the difference in the incidence of disease between oral contraceptive users and nonusers. The attributable risk does provide information about the actual occurrence of a disease in the population. For further information, the reader is referred to a text on epidemiologic methods.

1. THROMBOEMBOLIC DISORDERS AND OTHER VASCULAR PROBLEMS

a. Myocardial infarction

An increased risk of myocardial infarction has been attributed to oral contraceptive use. This risk is primarily in smokers or women with other underlying risk factors for coronary-artery disease such as hypertension, hypercholesterolemia, morbid obesity, and diabetes. The relative risk of heart attack for current oral contraceptive users has been estimated to be two to six. The risk is very low under the age of 30.

Smoking in combination with oral contraceptive use has been shown to contribute substantially to the incidence of myocardial infarctions in women in their mid-thirties or older with smoking accounting for the majority of excess cases. Mortality rates associated with circulatory disease have been shown to increase substantially in smokers over the age of 35 and nonsmokers over the age of 40 (Table IV) among women who use oral contraceptives.

TABLE IV. (Adapted from P.M. Layde and V. Beral) CIRCULATORY DISEASE MORTALITY RATES PER 100,000 WOMAN-YEARS BY AGE, SMOKING STATUS, AND ORAL CONTRACEPTIVE USE
AGE | EVER-USERS NON-SMOKERS | EVER-USERS SMOKERS | CONTROLS NON-SMOKERS | CONTROL SMOKERS
15-24 | 0.0 | 10.5 | 0.0 | 0.0
25-34 | 4.4 | 14.2 | 2.7 | 4.2
35-44 | 21.5 | 63.4 | 6.4 | 15.2
45+ | 52.4 | 206.7 | 11.4 | 27.9

Oral contraceptives may compound the effects of well-known risk factors, such as hypertension, diabetes, hyperlipidemias, age and obesity. In particular, some progestogens are known to decrease HDL cholesterol and cause glucose intolerance, while estrogens may create a state of hyperinsulinism. Oral contraceptives have been shown to increase blood pressure among users (see section 10 in "WARNINGS"). Similar effects on risk factors have been associated with an increased risk of heart disease. Oral contraceptives must be used with caution in women with cardiovascular disease risk factors.

b. Thromboembolism

An increased risk of thromboembolic and thrombotic disease associated with the use of oral contraceptives is well established. Case control studies have found the relative risk of users compared to nonusers to be 3 for the first episode of superficial venous thrombosis, 4 to 11 for deep vein thrombosis or pulmonary embolism, and 1.5 to 6 for women with predisposing conditions for venous thromboembolic disease. Cohort studies have shown the relative risk to be somewhat lower, about 3 for new cases and about 4.5 for new cases requiring hospitalization. The risk of thromboembolic disease due to oral contraceptives is not related to length of use and disappears after pill use is stopped.

A two- to four-fold increase in the relative risk of post-operative thromboembolic complications has been reported with the use of oral contraceptives. The relative risk of venous thrombosis in women who have predisposing conditions is twice that of women without such medical conditions. If feasible, oral contraceptives should be discontinued from at least four weeks prior to and for two weeks after elective surgery of a type associated with an increase in risk of thromboembolism and during and following prolonged immobilization. Since the immediate postpartum period is also associated with an increased risk of thromboembolism, oral contraceptives should be started no earlier than four to six weeks after delivery in women who elect not to breast-feed.

c. Cerebrovascular diseases

Oral contraceptives have been shown to increase both the relative and attributable risks of cerebrovascular events (thrombotic and hemorrhagic strokes), although, in general, the risk is greatest among older (>35 years), hypertensive women who also smoke. Hypertension was found to be a risk factor, for both users and nonusers, for both types of strokes, while smoking interacted to increase the risk for hemorrhagic strokes.

In a large study, the relative risk of thrombotic strokes has been shown to range from 3 for normotensive users to 14 for users with severe hypertension. The relative risk of hemorrhagic stroke is reported to be 1.2 for nonsmokers who used oral contraceptives, 2.6 for smokers who did not use oral contraceptives, 7.6 for smokers who used oral contraceptives, 1.8 for normotensive users and 25.7 for users with severe hypertension. The attributable risk is also greater in older women.

d. Dose-related risk of vascular disease from oral contraceptives

A positive association has been observed between the amount of estrogen and progestogen in oral contraceptives and the risk of vascular disease. A decline in serum high-density lipoproteins (HDL) has been reported with many progestational agents. A decline in serum high-density lipoproteins has been associated with an increased incidence of ischemic heart disease. Because estrogens increase HDL cholesterol, the net effect of an oral contraceptive depends on a balance achieved between doses of estrogen and progestogen and the nature and absolute amount of progestogen used in the contraceptive. The amount of both hormones should be considered in the choice of an oral contraceptive.

Minimizing exposure to estrogen and progestogen is in keeping with good principles of therapeutics. For any particular estrogen/progestogen combination, the dosage regimen prescribed should be one which contains the least amount of estrogen and progestogen that is compatible with a low failure rate and the needs of the individual patient. New acceptors of oral contraceptive agents should be started on preparations containing the lowest estrogen content which provides satisfactory results in the individual.

e. Persistence of risk of vascular disease

There are two studies which have shown persistence of risk of vascular disease for ever-users of oral contraceptives. In a study in the United States, the risk of developing myocardial infarction after discontinuing oral contraceptives persists for at least 9 years for women aged 40 to 49 years who had used oral contraceptives for five or more years, but this increased risk was not demonstrated in other age groups. In another study in Great Britain, the risk of developing cerebrovascular disease persisted for at least 6 years after discontinuation of oral contraceptives, although excess risk was very small. However, both studies were performed with oral contraceptive formulations containing 50 micrograms or higher of estrogens.

2. ESTIMATES OF MORTALITY FROM CONTRACEPTIVE USE

One study gathered data from a variety of sources which have estimated the mortality rate associated with different methods of contraception at different ages (Table V). These estimates include the combined risk of death associated with contraceptive methods plus the risk attributable to pregnancy in the event of method failure. Each method of contraception has its specific benefits and risks. The study concluded that with the exception of oral contraceptive users 35 and older who smoke and 40 and older who do not smoke, mortality associated with all methods of birth control is less than that associated with childbirth.

The observation of a possible increase in risk of mortality with age for oral contraceptive users is based on data gathered in the 1970's – but not reported until 1983. However, current clinical practice involves the use of lower estrogen dose formulations combined with careful restriction of oral contraceptive use to women who do not have the various risk factors listed in this labeling.

Because of these changes in practice and, also, because of some limited new data which suggest that the risk of cardiovascular disease with the use of oral contraceptives may now be less than previously observed, the Fertility and Maternal Health Drugs Advisory Committee was asked to review the topic in 1989. The Committee concluded that although cardiovascular disease risks may be increased with oral contraceptive use after age 40 in healthy nonsmoking women (even with the newer low-dose formulations), there are greater potential health risks associated with pregnancy in older women and with the alternative surgical and medical procedures which may be necessary if such women do not have access to effective and acceptable means of contraception.

Therefore, the Committee recommended that the benefits of oral contraceptive use by healthy nonsmoking women over 40 may outweigh the possible risks. Of course, older women, as all women who take oral contraceptives, should take the lowest possible dose formulation that is effective.

TABLE V. ANNUAL NUMBER OF BIRTH-RELATED OR METHOD-RELATED DEATHS ASSOCIATED WITH CONTROL OF FERTILITY PER 100,000 NONSTERILE WOMEN, BY FERTILITY-CONTROL METHOD ACCORDING TO AGE
Method of Control and Outcome | 15-19 | 20-24 | 25-29 | 30-34 | 35-39 | 40-44
No fertility control methods [Deaths are birth related] | 7.0 | 7.4 | 9.1 | 14.8 | 25.7 | 28.2
Oral contraceptives | 0.3 | 0.5 | 0.9 | 1.9 | 13.8 | 31.6
Non-smoker [Deaths are method related]
Oral contraceptives | 2.2 | 3.4 | 6.6 | 13.5 | 51.1 | 117.2
smoker
IUD | 0.8 | 0.8 | 1.0 | 1.0 | 1.4 | 1.4
Condom | 1.1 | 1.6 | 0.7 | 0.2 | 0.3 | 0.4
Diaphragm/Spermicide | 1.9 | 1.2 | 1.2 | 1.3 | 2.2 | 2.8
Periodic abstinence | 2.5 | 1.6 | 1.6 | 1.7 | 2.9 | 3.6
Adapted from H.W. Ory, Family Planning Perspectives 15:57-63, 1983

3. MALIGNANT NEOPLASMS

Breast Cancer

Sronyx is contraindicated in females who currently have or have had breast cancer because breast cancer may be hormonally sensitive [see CONTRAINDICATIONS].

Epidemiology studies have not found a consistent association between use of combined oral contraceptives (COCs) and breast cancer risk. Studies do not show an association between ever (current or past) use of COCs and risk of breast cancer. However, some studies report a small increase in the risk of breast cancer among current or recent users (<6 months since last use) and current users with longer duration of COC use [see Postmarketing Experience].

Cervical Cancer

Some studies suggest that oral contraceptive use has been associated with an increase in the risk of cervical intraepithelial neoplasia in some populations of women. However, there continues to be controversy about the extent to which such findings may be due to differences in sexual behavior and other factors.

In spite of many studies of the relationship between oral contraceptive use and breast and cervical cancers, a cause-and-effect relationship has not been established.

4. HEPATIC NEOPLASIA

Benign hepatic adenomas are associated with oral contraceptive use, although the incidence of benign tumors is rare in the United States. Indirect calculations have estimated the attributable risk to be in the range of 3.3 cases/100,000 for users, a risk that increases after four or more years of use. Rupture of rare, benign, hepatic adenomas may cause death through intra-abdominal hemorrhage.

Studies from Britain have shown an increased risk of developing hepatocellular carcinoma in long-term (>8 years) oral contraceptive users. However, these cancers are extremely rare in the U.S. and the attributable risk (the excess incidence) of liver cancers in oral contraceptive users approaches less than one per million users.

5. RISK OF LIVER ENZYME ELEVATIONS WITH CONCOMITANT HEPATITIS C TREATMENT

During clinical trials with the Hepatitis C combination drug regimen that contains ombitasvir/paritaprevir/ritonavir, with or without dasabuvir, ALT elevations greater than 5 times the upper limit of normal (ULN), including some cases greater than 20 times the ULN, were significantly more frequent in women using ethinyl estradiol-containing medications such as COCs. Discontinue Sronyx prior to starting therapy with the combination drug regimen ombitasvir/paritaprevir/ritonavir, with or without dasabuvir [see Contraindications (4)] . Sronyx can be restarted approximately 2 weeks following completion of treatment with the combination drug regimen.

6. OCULAR LESIONS

There have been clinical case reports of retinal thrombosis associated with the use of oral contraceptives. Oral contraceptives should be discontinued if there is unexplained partial or complete loss of vision; onset of proptosis or diplopia; papilledema; or retinal vascular lesions. Appropriate diagnostic and therapeutic measures should be undertaken immediately.

7. ORAL CONTRACEPTIVE USE BEFORE OR DURING EARLY PREGNANCY

Extensive epidemiological studies have revealed no increased risk of birth defects in women who have used oral contraceptives prior to pregnancy. Studies also do not suggest a teratogenic effect, particularly insofar as cardiac anomalies and limb-reduction defects are concerned, when taken inadvertently during early pregnancy. The administration of oral contraceptives to induce withdrawal bleeding should not be used as a test for pregnancy. Oral contraceptives should not be used during pregnancy to treat threatened or habitual abortion. It is recommended that for any patient who has missed two consecutive periods, pregnancy should be ruled out before continuing oral contraceptive use. If the patient has not adhered to the prescribed schedule, the possibility of pregnancy should be considered at the time of the first missed period. Oral contraceptive use should be discontinued if pregnancy is confirmed.

8. GALLBLADDER DISEASE

Earlier studies have reported an increased lifetime relative risk of gallbladder surgery in users of oral contraceptives and estrogens. More recent studies, however, have shown that the relative risk of developing gallbladder disease among oral contraceptive users may be minimal. The recent findings of minimal risk may be related to the use of oral contraceptive formulations containing lower hormonal doses of estrogens and progestogens.

9. CARBOHYDRATE AND LIPID METABOLIC EFFECTS

Oral contraceptives have been shown to cause glucose intolerance in a significant percentage of users. Oral contraceptives containing greater than 75 micrograms of estrogens cause hyperinsulinism, while lower doses of estrogen cause less glucose intolerance. Progestogens increase insulin secretion and create insulin resistance, this effect varying with different progestational agents. However, in the nondiabetic woman, oral contraceptives appear to have no effect on fasting blood glucose. Because of these demonstrated effects, prediabetic and diabetic women should be carefully observed while taking oral contraceptives.

A small proportion of women will have persistent hypertriglyceridemia while on the pill. As discussed earlier (see "WARNINGS" 1a.and 1d.), changes in serum triglycerides and lipoprotein levels have been reported in oral contraceptive users.

10. ELEVATED BLOOD PRESSURE

An increase in blood pressure has been reported in women taking oral contraceptives and this increase is more likely in older oral contraceptive users and with continued use. Data from the Royal College of General Practitioners and subsequent randomized trials have shown that the incidence of hypertension increases with increasing quantities of progestogens.

Women with a history of hypertension or hypertension-related diseases, or renal disease should be encouraged to use another method of contraception. If women with hypertension elect to use oral contraceptives, they should be monitored closely, and if significant elevation of blood pressure occurs, oral contraceptives should be discontinued. For most women, elevated blood pressure will return to normal after stopping oral contraceptives, and there is no difference in the occurrence of hypertension among ever- and never-users.

11. HEADACHE

The onset or exacerbation of migraine or development of headache with a new pattern which is recurrent, persistent or severe requires discontinuation of oral contraceptives and evaluation of the cause.

12. BLEEDING IRREGULARITIES

Breakthrough bleeding and spotting are sometimes encountered in patients on oral contraceptives, especially during the first three months of use. Nonhormonal causes should be considered and adequate diagnostic measures taken to rule out malignancy or pregnancy in the event of breakthrough bleeding, as in the case of any abnormal vaginal bleeding. If pathology has been excluded, time or a change to another formulation may solve the problem. In the event of amenorrhea, pregnancy should be ruled out.

Some women may encounter post-pill amenorrhea or oligomenorrhea, especially when such a condition was pre-existent.

PRECAUTIONS

1. GENERAL

Patients should be counseled that this product does not protect against HIV infection (AIDS) and other sexually transmitted diseases.

2. PHYSICAL EXAMINATION AND FOLLOW-UP

It is good medical practice for all women to have annual history and physical examinations, including women using oral contraceptives. The physical examination, however, may be deferred until after initiation of oral contraceptives if requested by the woman and judged appropriate by the clinician. The physical examination should include special reference to blood pressure, breasts, abdomen and pelvic organs, including cervical cytology and relevant laboratory tests. In case of undiagnosed, persistent or recurrent abnormal vaginal bleeding, appropriate measures should be conducted to rule out malignancy. Women with a strong family history of breast cancer or who have breast nodules should be monitored with particular care.

3. LIPID DISORDERS

Women who are being treated for hyperlipidemias should be followed closely if they elect to use oral contraceptives. Some progestogens may elevate LDL levels and may render the control of hyperlipidemias more difficult.

4. LIVER FUNCTION

If jaundice develops in any woman receiving such drugs, the medication should be discontinued. Steroid hormones may be poorly metabolized in patients with impaired liver function.

5. FLUID RETENTION

Oral contraceptives may cause some degree of fluid retention. They should be prescribed with caution, and only with careful monitoring, in patients with conditions which might be aggravated by fluid retention.

6. EMOTIONAL DISORDERS

Women with a history of depression should be carefully observed and the drug discontinued if depression recurs to a serious degree.

7. CONTACT LENSES

Contact-lens wearers who develop visual changes or changes in lens tolerance should be assessed by an ophthalmologist.

8. DRUG INTERACTIONS

Reduced efficacy and increased incidence of breakthrough bleeding and menstrual irregularities have been associated with concomitant use of rifampin. A similar association, though less marked, has been suggested with barbiturates, phenylbutazone, phenytoin sodium, and possibly with griseofulvin, ampicillin and tetracyclines.

Concomitant Use with HCV Combination Therapy – Liver Enzyme Elevation

Do not co-administer Sronyx with HCV drug combinations containing ombitasvir/paritaprevir/ritonavir, with or without dasabuvir, due to potential for ALT elevations (see Warnings, RISK OF LIVER ENZYME ELEVATIONS WITH CONCOMITANT HEPATITIS C TREATMENT).

9. INTERACTIONS WITH LABORATORY TESTS

Certain endocrine- and liver-function tests and blood components may be affected by oral contraceptives:

1. Increased prothrombin and factors VII, VIII, IX and X; decreased antithrombin 3; increased norepinephrine-induced platelet aggregability.
2. Increased thyroid-binding globulin (TBG) leading to increased circulating total thyroid hormone, as measured by protein-bound iodine (PBI), T4 by column or by radioimmunoassay. Free T3 resin uptake is decreased, reflecting the elevated TBG, free T4 concentration is unaltered.
3. Other binding proteins may be elevated in serum.
4. Sex-binding globulins are increased and result in elevated levels of total circulating sex steroids and corticoids; however, free or biologically active levels remain unchanged.
5. Triglycerides may be increased.
6. Glucose tolerance may be decreased.
7. Serum folate levels may be depressed by oral contraceptive therapy. This may be of clinical significance if a woman becomes pregnant shortly after discontinuing oral contraceptives.

10. CARCINOGENESIS

See " WARNINGS" section.

11. PREGNANCY

See " CONTRAINDICATIONS" and " WARNINGS" sections.

12. NURSING MOTHERS

Small amounts of oral contraceptive steroids have been identified in the milk of nursing mothers, and a few adverse effects on the child have been reported, including jaundice and breast enlargement. In addition, oral contraceptives given in the postpartum period may interfere with lactation by decreasing the quantity and quality of breast milk. If possible, the nursing mother should be advised not to use oral contraceptives but to use other forms of contraception until she has completely weaned her child.

13. PEDIATRIC USE

Safety and efficacy of Levonorgestrel and Ethinyl Estradiol Tablets USP have been established in women of reproductive age. Safety and efficacy are expected to be the same for postpubertal adolescents under the age of 16 and for users 16 years and older. Use of this product before menarche is not indicated.

INFORMATION FOR THE PATIENT

See " Patient Labeling" printed below.

ADVERSE REACTIONS

Post Marketing Experience

Five studies that compared breast cancer risk between ever-users (current or past use) of COCs and never-users of COCs reported no association between ever use of COCs and breast cancer risk, with effect estimates ranging from 0.90 – 1.12 (Figure 2).

Three studies compared breast cancer risk between current or recent COC users (,6 months since last use) and never users of COCs (Figure 2). One of these studies reported no association between breast cancer risk and COC use. The other two studies found an increased relative risk of 1.19 – 1.33 with current or recent use. Both of these studies found an increased risk of breast cancer with current use of longer duration, with relative risks ranging from 1.03 with less than one year of COC use to approximate 1.4 with more than 8-10 years of COC use.

Figure 2: Risk of Breast Cancer with Combined Oral Contraceptive Use

RR = relative risk; OR = odds ratio; HR = hazard ratio. "ever COC" are females with current or past COC use; "never COC use" are females that never used COCs.

An increased risk of the following serious adverse reactions has been associated with the use of oral contraceptives (see " WARNINGS" section).

- Thrombophlebitis
- Arterial thromboembolism
- Pulmonary embolism
- Myocardial infarction
- Cerebral hemorrhage
- Cerebral thrombosis
- Hypertension
- Gallbladder disease
- Hepatic adenomas or benign liver tumors

There is evidence of an association between the following conditions and the use of oral contraceptives, although additional confirmatory studies are needed:

- Mesenteric thrombosis
- Retinal thrombosis

The following adverse reactions have been reported in patients receiving oral contraceptives and are believed to be drug related:

- Nausea
- Vomiting
- Gastrointestinal symptoms, (such as abdominal cramps and bloating)
- Breakthrough bleeding
- Spotting
- Change in menstrual flow
- Amenorrhea
- Temporary infertility after discontinuation of treatment
- Edema
- Melasma which may persist
- Breast changes: tenderness, enlargement, secretion
- Change in weight (increase or decrease)
- Change in cervical erosion and secretion
- Diminution in lactation when given immediately postpartum
- Cholestatic jaundice
- Migraine
- Rash (allergic)
- Mental depression
- Reduced tolerance to carbohydrates
- Vaginal candidiasis
- Change in corneal curvature (steepening)
- Intolerance to contact lenses

The following adverse reactions have been reported in users of oral contraceptives and the association has been neither confirmed nor refuted:

- Pre-menstrual syndrome
- Cataracts
- Optic neuritis
- Changes in appetite
- Cystitis-like syndrome
- Headache
- Nervousness
- Dizziness
- Hirsutism
- Loss of scalp hair
- Erythema multiforme
- Erythema nodosum
- Hemorrhagic eruption
- Vaginitis
- Porphyria
- Impaired renal function
- Hemolytic uremic syndrome
- Budd-Chiari syndrome
- Acne
- Changes in libido
- Colitis

OVERDOSAGE

Serious ill effects have not been reported following acute ingestion of large doses of oral contraceptives by young children. Overdosage may cause nausea, and withdrawal bleeding may occur in females.

NON-CONTRACEPTIVE HEALTH BENEFITS

The following non-contraceptive health benefits related to the use of oral contraceptives are supported by epidemiological studies which largely utilized oral contraceptive formulations containing doses exceeding 0.035 mg of ethinyl estradiol or 0.05 mg mestranol.

Effects on menses:

- increased menstrual cycle regularity
- decreased blood loss and decreased incidence of iron-deficiency anemia
- decreased incidence of dysmenorrhea

Effects related to inhibition of ovulation:

- decreased incidence of functional ovarian cysts
- decreased incidence of ectopic pregnancies

Effects from long-term use:

- decreased incidence of fibroadenomas and fibrocystic disease of the breast
- decreased incidence of acute pelvic inflammatory disease
- decreased incidence of endometrial cancer
- decreased incidence of ovarian cancer

DOSAGE AND ADMINISTRATION

Sronyx®(Levonorgestrel and Ethinyl Estradiol Tablets USP)

To achieve maximum contraceptive effectiveness, Sronyx must be taken exactly as directed at intervals not exceeding 24-hours.

Sronyx is a monophasic preparation plus 7 inert tablets. The dosage of Sronyx is one tablet daily for 21 consecutive days per menstrual cycle plus 7 peach inert tablets according to the prescribed schedule. It is recommended that Sronyx be taken at the same time each day, preferably after the evening meal or at bedtime. During the first cycle of medication, the patient should be instructed to take one white Sronyx tablet daily and then 7 peach inert tablets for twenty-eight (28) consecutive days, beginning on day one (1) of her menstrual cycle. (The first day of menstruation is day one.) Withdrawal bleeding usually occurs within 3 days following the last white tablet. (If Sronyx is first taken later than the first day of the first menstrual cycle of medication or postpartum, contraceptive reliance should not be placed on Sronyx until after the first 7 consecutive days of administration. The possibility of ovulation and conception prior to initiation of medication should be considered.)

When switching from another oral contraceptive, Sronyx should be started on the first day of bleeding following the last active tablet taken of the previous oral contraceptive. The patient begins her next and all subsequent 28-day courses of Sronyx on the same day of the week that she began her first course, following the same schedule. She begins taking her white tablets on the next day after ingestion of the last peach tablet, regardless of whether or not a menstrual period has occurred or is still in progress.

Anytime a subsequent cycle of Sronyx is started later than the next day, the patient should be protected by another means of contraception until she has taken a tablet daily for seven consecutive days.

If spotting or breakthrough bleeding occurs, the patient is instructed to continue on the same regimen. This type of bleeding is usually transient and without significance, however, if the bleeding is persistent or prolonged, the patient is advised to consult her physician. Although the occurrence of pregnancy is highly unlikely if Sronyx is taken according to directions, if withdrawal bleeding does not occur, the possibility of pregnancy must be considered. If the patient has not adhered to the prescribed schedule (missed one or more active tablets or started taking them on a day later than she should have), the probability of pregnancy should be considered at the time of the first missed period and appropriate diagnostic measures taken before the medication is resumed. If the patient has adhered to the prescribed regimen and misses two consecutive periods, pregnancy should be ruled out before continuing the contraceptive regimen.

The risk of pregnancy increases with each active (white) tablet missed. For additional patient instructions regarding missed pills, see the "WHAT TO DO IF YOU MISS PILLS" section in the DETAILED PATIENT LABELINGbelow. If breakthrough bleeding occurs following missed tablets, it will usually be transient and of no consequence. If the patient misses one or more peach tablets, she is still protected against pregnancy provided she begins taking white tablets again on the proper day.

In the nonlactating mother, Sronyx may be initiated postpartum, for contraception. When the tablets are administered in the postpartum period, the increased risk of thromboembolic disease associated with the postpartum period must be considered. (See " CONTRAINDICATIONS, " " WARNINGS, "and PRECAUTIONS" concerning thromboembolic disease.) It is to be noted that early resumption of ovulation may occur if bromocriptine mesylate has been used for the prevention of lactation.

HOW SUPPLIED

Sronyx®is available in a 28 Tablet Dispenser, arranged in 3 rows of 7 active tablets and 1 row of inert tablets, as follows:

21 active tablets: white, round tablet debossed with "WATSON" on one side and "967" on the other side. 7 inert tablets: peach, round tablet debossed with "WATSON" on one side and "P1" on the other side.

STORAGE AND HANDLING

Store at 20° to 25°C (68° to 77°F). [See USP Controlled Room Temperature.]

PATIENT INFORMATION

BRIEF SUMMARY
PATIENT PACKAGE INSERT
This product (like all oral contraceptives) is intended to prevent pregnancy. It does not protect against HIV infection (AIDS) and other sexually transmitted diseases.

Oral contraceptives, also known as "birth-control pills" or "the pill", are taken to prevent pregnancy, and when taken correctly, have a failure rate of less than 1% per year when used without missing any pills. The typical failure rate of large numbers of pill users is less than 3% per year when women who miss pills are included. For most women oral contraceptives are also free of serious or unpleasant side effects. However, forgetting to take pills considerably increases the chances of pregnancy.

For the majority of women, oral contraceptives can be taken safely. But there are some women who are at high risk of developing certain serious diseases that can be life-threatening or may cause temporary or permanent disability or death. The risks associated with taking oral contraceptives increase significantly if you:

- smoke
- have high blood pressure, diabetes, high cholesterol
- have or have had clotting disorders, heart attack, stroke, angina pectoris, cancer of the breast or sex organs, jaundice, or malignant or benign liver tumors.

You should not take the pill if you suspect you are pregnant or have unexplained vaginal bleeding.

Cigarette smoking increases the risk of serious adverse effects on the heart and blood vessels from oral contraceptive use. This risk increases with age and with heavy smoking (15 or more cigarettes per day) and is quite marked in women over 35 years of age. Women who use oral contraceptives should not smoke.

Most side effects of the pill are not serious. The most common such effects are nausea, vomiting, bleeding between menstrual periods, weight gain, breast tenderness, and difficulty wearing contact lenses. These side effects, especially nausea and vomiting, may subside within the first three months of use.

The serious side effects of the pill occur very infrequently, especially if you are in good health and are young. However, you should know that the following medical conditions have been associated with or made worse by the pill:

1. Blood clots in the legs (thrombophlebitis), lungs (pulmonary embolism), stoppage or rupture of a blood vessel in the brain (stroke), blockage of blood vessels in the heart (heart attack and angina pectoris) or other organs of the body. As mentioned above, smoking increases the risk of heart attacks and strokes and subsequent serious medical consequences.
2. Liver tumors, which may rupture and cause severe bleeding. A possible but not definite association has been found with the pill and liver cancer. However, liver cancers are extremely rare. The chance of developing liver cancer from using the pill is thus even rarer.
3. High blood pressure, although blood pressure usually returns to normal when the pill is stopped.

The symptoms associated with these serious side effects are discussed in the detailed leaflet given to you with your supply of pills. Notify your doctor or healthcare provider if you notice any unusual physical disturbances while taking the pill. In addition, drugs such as rifampin, as well as some anticonvulsants and some antibiotics, may decrease oral contraceptive effectiveness.

There may be slight increases in the risk of breast cancer among current users of hormonal birth control pills with longer duration of uses of 8 years or more.

Taking the pill provides some important non-contraceptive benefits. These include less painful menstruation, less menstrual blood loss and anemia, fewer pelvic infections, and fewer cancers of the ovary and the lining of the uterus.

Be sure to discuss any medical condition you may have with your healthcare provider. Your healthcare provider will take a medical and family history before prescribing oral contraceptives and will examine you. The physical examination may be delayed to another time if you request it and the healthcare provider believes that it is appropriate to postpone it. You should be reexamined at least once a year while taking oral contraceptives. The detailed patient information booklet gives you further information which you should read and discuss with your healthcare provider.

This product (like all oral contraceptives) is intended to prevent pregnancy. It does not protect against HIV infection (AIDS) and other sexually transmitted diseases such as chlamydia, genital herpes, genital warts, gonorrhea, hepatitis B, and syphilis.

INSTRUCTIONS TO PATIENTS
HOW TO TAKE THE PILL

IMPORTANT POINTS TO REMEMBER

BEFOREYOU START TAKING YOUR PILLS:

1. BE SURE TO READ THESE DIRECTIONS:
  Before you start taking your pills.
  Anytime you are not sure what to do.
2. THE RIGHT WAY TO TAKE THE PILL IS TO TAKE ONE PILL EVERY DAY AT THE SAME TIME.
  If you miss pills you could get pregnant. This includes starting the pack late. The more pills you miss, the more likely you are to get pregnant.
3. MANY WOMEN HAVE SPOTTING OR LIGHT BLEEDING, OR MAY FEEL SICK TO THEIR STOMACH DURING THE FIRST 1–3 PACKS OF PILLS.
  If you do feel sick to your stomach, do not stop taking the pill. The problem will usually go away. If it does not go away, check with your doctor or clinic.
4. MISSING PILLS CAN ALSO CAUSE SPOTTING OR LIGHT BLEEDING, even when you make up these missed pills.
  On the days you take two pills, to make up for missed pills, you could also feel a little sick to your stomach.
5. IF YOU HAVE VOMITING OR DIARRHEA, for any reason, or IF YOU TAKE SOME MEDICINES, including some antibiotics, your pills may not work as well.
  Use a back-up method (such as condoms, foam, or sponge) until you check with your doctor or clinic.
6. IF YOU HAVE TROUBLE REMEMBERING TO TAKE THE PILL, talk to your doctor or clinic about how to make pill-taking easier or about using another method of birth control.
7. IF YOU HAVE ANY QUESTIONS OR ARE UNSURE ABOUT THE INFORMATION IN THIS LEAFLET, call your doctor or clinic.

BEFOREYOU START TAKING YOUR PILLS

1. DECIDE WHAT TIME OF DAY YOU WANT TO TAKE YOUR PILL.
  It is important to take it at about the same time every day.
2. LOOK AT YOUR PILL PACK:
  The 28-pillpack has 21 (white) "active" pills (with hormones) to take for three weeks, followed by 1 week of reminder pills (peach) (without hormones).
3. ALSO FIND:
  - where on the pack to start taking pills,
  - in what order to take the pills (follow the arrows)
  - the week numbers as shown in picture below.
4. BE SURE YOU HAVE READY AT ALL TIMES:
  ANOTHER KIND OF BIRTH CONTROL (such as condoms, foam or sponge) to use as a back-up in case you miss pills.
  AN EXTRA, FULL PILL PACK.

WHEN TO START THE FIRSTPACK OF PILLS

You have a choice for which day to start taking your first pack of pills. Decide with your doctor or clinic which is the best day for you. Pick a time of day which will be easy to remember.

DAY 1 START:

- Pick the day label strip that starts with the first day of your period. Place this day label strip over the area that has the days of the week (starting with Sunday) pre-printed on the tablet dispenser.

Note: If the first day of your period is a Sunday, you can skip step #1.

- Take the first (white) "active" pill of the first pack during the first 24 hours of your period.
- You will not need to use a back-up method of birth control, since you are starting the pill at the beginning of your period.

SUNDAY START:

1. Take the first (white) "active" pill of the first pack on the Sunday after your period starts, even if you are still bleeding. If your period begins on Sunday, start the pack that same day.
2. Use another method of birth controlas a back-up method if you have sex anytime from the Sunday you start your first pack until the next Sunday (7 days). Condoms, foam, or the sponge are good back-up methods of birth control.

WHAT TO DO DURING THE MONTH

- TAKE ONE PILL AT THE SAME TIME EVERY DAY UNTIL THE PACK IS EMPTY
  Do not skip pills even if you are spotting or bleeding between monthly periods or feel sick to your stomach (nausea).
  Do not skip pills even if you do not have sex very often.
- WHEN YOU FINISH A PACK OR SWITCH YOUR BRAND OF PILLS:
  28 pills: Start the next pack on the day after your last (peach) "reminder" pill. Do not wait any days between packs.

WHAT TO DO IF YOU MISS PILLS

If you MISS 1(white) "active" pill:

1. Take it as soon as you remember. Take the next pill at your regular time. This means you may take two pills in one day.
2. You do not need to use a back-up birth control method if you have sex.

If you MISS 2(white) "active" pills in a row in WEEK 1 OR WEEK 2of your pack:

1. Take two pills on the day you remember and two pills the next day.
2. Then take one pill a day until you finish the pack.
3. You MAY BECOME PREGNANT if you have sex in the 7 days after you miss pills. You MUST use another birth control method (such as condoms, foam, or sponge) as a back-up for those 7 days.

If you MISS 2(white) "active" pills in a row in THE 3rd WEEK:

1. If you are a Day 1 Starter:
  THROW OUT the rest of the pill pack and start a new pack that same day.
  If you are a Sunday Starter:
  Keep taking one pill every day until Sunday. On Sunday, THROW OUT the rest of the pack and start a new pack of pills that same day.
2. You may not have your period this month but this is expected.
  However, if you miss your period two months in a row, call your doctor or clinic because you might be pregnant.
3. You MAY BECOME PREGNANT if you have sex in the 7 days after you miss pills. You MUST use another birth control method (such as condoms, foam, or sponge) as a back-up for those 7 days.

If you MISS 3 OR MORE(white) "active" pills in a row (during the first 3 weeks).

- If you are a Day 1 Starter:
  THROW OUT the rest of the pill pack and start a new pack that same day.
  If you are a Sunday Starter:
  Keep taking 1 pill every day until Sunday. On Sunday, THROW OUT the rest of the pack and start a new pack of pills that same day.
- You may not have your period this month but this is expected. However, if you miss your period two months in a row, call your doctor or clinic because you might be pregnant.
- You MAY BECOME PREGNANT if you have sex in the 7 days after you miss pills. You MUST use another birth control method (such as condoms, foam, or sponge) as a back-up for those 7 days.

A REMINDER FOR THOSE ON 28-DAY PACKS:

If you forget any of the 7 (peach) "reminder" pills in Week 4:

THROW AWAY the pills you missed.

Keep taking one pill each day until the pack is empty. You do not need a back-up method.

FINALLY, IF YOU ARE STILL NOT SURE WHAT TO DO ABOUT THE PILLS YOU HAVE MISSED:

Use a BACK-UP METHOD anytime you have sex.

KEEP TAKING ONE ACTIVE PILL EACH DAY until you can reach your doctor or clinic.

DETAILED PATIENT PACKAGE INSERT
This product (like all oral contraceptives) is intended to prevent pregnancy.
It does not protect against HIV infection (AIDS) and other sexually transmitted diseases.

INTRODUCTION

Any woman who considers using oral contraceptives (the "birth-control pill" or "the "pill") should understand the benefits and risks of using this form of birth control. This leaflet will give you much of the information you will need to make this decision and will also help you determine if you are at risk of developing any of the serious side effects of the pill. It will tell you how to use the pill properly so that it will be as effective as possible. However, this leaflet is not a replacement for a careful discussion between you and your healthcare provider. You should discuss the information provided in this leaflet with him or her, both when you first start taking the pill and during your revisits. You should also follow your healthcare provider's advice with regard to regular check-up while you are on the pill.

EFFECTIVENESS OF ORAL CONTRACEPTIVES

Oral contraceptives or "birth-control pills" or "the pill" are used to prevent pregnancy and are more effective than other nonsurgical methods of birth control. When they are taken correctly, the chance of becoming pregnant is less than 1.0% when used perfectly, without missing any pills. Typical failure rates are less than 3.0% per year. The chance of becoming pregnant increases with each missed pill during a menstrual cycle.

In comparison, typical failure rates for other nonsurgical methods of birth control during the first year of use are as follows:

Percentage of women experiencing an unintended pregnancy during the first year of typical use and first year of perfect use of contraception and the percentage continuing use at the end of the first year. United States.
 | % of Women Experiencing an Accidental Pregnancy within the First Year of Use |  | % of Women Continuing Use at One Year [Among couples attempting to avoid pregnancy, the percentage who continue to use a method for one year.]
Method (1) | Typical Use [Among typical couples who initiate use of a method (not necessarily for the first time), the percentage who experience an accidental pregnancy during the first year if they do not stop use for any other reason.] (2) | Perfect Use [Among couples who initiate use of a method (not necessarily for the first time) and who use it perfectly (both consistently and correctly), the percentage who experience an accidental pregnancy during the first year if they do not stop use for any other reason.] (3) | (4)
Chance | 85 | 85
Spermicides [Foams, creams, gels, vaginal suppositories, vaginal film.] | 26 | 6 | 40
Periodic abstinence | 25 |  | 63
Calendar |  | 9
Ovulation method |  | 3
Sympto-thermal [Cervical mucus (ovulation) method supplemented by calendar in the pre-ovulatory and basal body temperature in the post-ovulatory phases.] |  | 2
Post Ovulation |  | 1
Withdrawal | 19 | 4
Cap [With spermicidal cream or jelly.]
Parous women | 40 | 26 | 42
Nulliparous women | 20 | 9 | 56
Sponge
Parous women | 40 | 20 | 42
Nulliparous women | 20 | 9 | 56
Diaphragm | 20 | 6 | 56
Condom [Without spermicides.]
Female (Reality) | 21 | 5 | 56
Male | 14 | 3 | 61
Pill | 5 |  | 71
Progestin only |  | 0.5
Combined |  | 0.1
IUD
Progesterone T | 2 | 1.5 | 81
Copper T380A | 0.8 | 0.6 | 78
Lng 20 | 0.1 | 0.1 | 81
Depo Provera | 0.3 | 0.3 | 70
Norplant and Norplant-2 | 0.05 | 0.05 | 88
Female sterilization | 0.5 | 0.5 | 100
Male sterilization | 0.15 | 0.10 | 100
Source: Trussell J, Contraceptive efficacy. In Hatcher RA, Trussell J, Stewart F, Cates W, Stewart GK, Kowal D, Guest F, Contraceptive Technology: Seventeenth Revised Edition.New York NY: Irvington Publishers, 1998.
4 The percentages becoming pregnant in columns (2) and (3) are based on data from populations where contraception is not used and from women who cease using contraception in order to become pregnant. Among such populations, about 89% become pregnant within one year. This estimate was lowered slightly (to 85%) to represent the percentage who would become pregnant within one year among women now relying on reversible methods of contraception if they abandoned contraception altogether.

WHO SHOULD NOT TAKE ORAL CONTRACEPTIVES

Cigarette smoking increases the risk of serious adverse effects on the heart and blood vessels from oral contraceptive use. This risk increases with age and with heavy smoking (15 or more cigarettes per day) and is quite marked in women over 35 years of age. Women who use oral contraceptives should not smoke.

Some women should not use the pill. For example, you should not take the pill if you are pregnant or think you may be pregnant. You should also not use the pill if you have had any of the following conditions:

- A history of heart attack or stroke
- Blood clots in the legs (thrombophlebitis), lungs (pulmonary embolism), or eyes
- A history of blood clots in the deep veins of your legs
- Chest pain (angina pectoris)
- Known or suspected breast cancer or cancer of the lining of the uterus, cervix or vagina
- Unexplained vaginal bleeding (until a diagnosis is reached by your doctor)
- Yellowing of the whites of the eyes or of the skin (jaundice) during pregnancy or during previous use of the pill
- Liver tumor (benign or cancerous)
- Take any Hepatitis C drug combination containing ombitasvir/paritaprevir/ritonavir, with or without dasabuvir. This may increase levels of the liver enzyme "alanine aminotransferase" (ALT) in the blood.
- Known or suspected pregnancy

Tell your healthcare provider if you have ever had any of these conditions. Your healthcare provider can recommend another method of birth control.

OTHER CONSIDERATIONS BEFORE TAKING ORAL CONTRACEPTIVES

Tell your healthcare provider if you or any family member has ever had:

- Breast nodules, fibrocystic disease of the breast, an abnormal breast X-ray or mammogram
- Diabetes
- Elevated cholesterol or triglycerides
- High blood pressure
- Migraine or other headaches or epilepsy
- Mental depression
- Gallbladder, heart or kidney disease
- History of scanty or irregular menstrual periods

Women with any of these conditions should be checked often by their healthcare provider if they choose to use oral contraceptives.

Also, be sure to inform your doctor or healthcare provider if you smoke or are on any medications.

RISKS OF TAKING ORAL CONTRACEPTIVES

1. RISK OF DEVELOPING BLOOD CLOTS

Blood clots and blockage of blood vessels are the most serious side effects of taking oral contraceptives and can be fatal. In particular, a clot in the legs can cause thrombophlebitis and a clot that travels to the lungs can cause sudden blocking of the vessel carrying blood to the lungs. Rarely, clots occur in the blood vessels of the eye and may cause blindness, double vision, or impaired vision.

If you take oral contraceptives and need elective surgery, need to stay in bed for a prolonged illness or have recently delivered a baby, you may be at risk of developing blood clots. You should consult your doctor about stopping oral contraceptives three to four weeks before surgery and not taking oral contraceptives for two weeks after surgery or during bed rest. You should also not take oral contraceptives soon after delivery of a baby or a mid-trimester pregnancy termination. It is advisable to wait for at least four weeks after delivery if you are not breast-feeding. If you are breast-feeding, you should wait until you have weaned your child before using the pill. (See also the section on breast-feeding in "GENERAL PRECAUTIONS".)

2. HEART ATTACKS AND STROKES

Oral contraceptives may increase the tendency to develop strokes (stoppage or rupture of blood vessels in the brain) and angina pectoris and heart attacks (blockage of blood vessels in the heart). Any of these conditions can cause death or serious disability.

Smoking greatly increases the possibility of suffering heart attacks and strokes. Furthermore, smoking and the use of oral contraceptives greatly increase the chances of developing and dying of heart disease.

3. GALLBLADDER DISEASE

Oral contraceptive users probably have a greater risk than nonusers of having gallbladder disease, although this risk may be related to pills containing high doses of estrogens.

4. LIVER TUMORS

ln rare cases, oral contraceptives can cause benign but dangerous liver tumors. These benign liver tumors can rupture and cause fatal internal bleeding. ln addition, a possible but not definite association has been found with the pill and liver cancers in two studies, in which a few women who developed these very rare cancers were found to have used oral contraceptives for long periods. However, liver cancers are extremely rare. The chance of developing liver cancer from using the pill is thus even rarer.

5. RISK OF CANCER

It is not known if hormonal birth control pills cause breast cancer. Some studies, but not all, suggest that there could be a slight increase in the risk of breast cancer among current users with longer duration of use.

If you have breast cancer now, or have had it in the past, do not use hormonal birth control because some breast cancers are sensitive to hormones.

Some studies have found an increase in the incidence of cancer of the cervix in women who use oral contraceptives. However, this finding may be related to factors other than the use of oral contraceptives.

TABLE V. ANNUAL NUMBER OF BIRTH-RELATED OR METHOD-RELATED DEATHS ASSOCIATED WITH CONTROL OF FERTILITY PER 100,000 NONSTERILE WOMEN, BY FERTILITY-CONTROL METHOD ACCORDING TO AGE
Method of Control and Outcome | 15-19 | 20-24 | 25-29 | 30-34 | 35-39 | 40-44
No fertility | 7.0 | 7.4 | 9.1 | 14.8 | 25.7 | 28.2
control methods [Deaths are birth related]
Oral contraceptives | 0.3 | 0.5 | 0.9 | 1.9 | 13.8 | 31.6
Non-smoker [Deaths are method related]
Oral contraceptives | 2.2 | 3.4 | 6.6 | 13.5 | 51.1 | 117.2
smoker
IUD | 0.8 | 0.8 | 1.0 | 1.0 | 1.4 | 1.4
Condom | 1.1 | 1.6 | 0.7 | 0.2 | 0.3 | 0.4
Diaphragm/Spermicide | 1.9 | 1.2 | 1.2 | 1.3 | 2.2 | 2.8
Periodic abstinence | 2.5 | 1.6 | 1.6 | 1.7 | 2.9 | 3.6
Adapted from H.W. Ory, Family Planning Perspectives 15:57-63, 1983

In the above table, the risk of death from any birth-control method is less than the risk of childbirth, except for oral contraceptive users over the age of 35 who smoke and pill users over the age of 40 even if they do not smoke. It can be seen in the table that for women aged 15 to 39, the risk of death was highest with pregnancy (7-26 deaths per 100,000 women, depending on age). Among pill users who do not smoke, the risk of death was always lower than that associated with pregnancy for any age group, except for those women over the age of 40, when the risk increases to 32 deaths per 100,000 women, compared to 28 associated with pregnancy at that age. However, for pill users who smoke and are over the age of 35, the estimated number of deaths exceeds those for other methods of birth control. If a woman is over the age of 40 and smokes, her estimated risk of death is four times higher (117/100,000 women) than the estimated risk associated with pregnancy (28/100,000 women) in that age group.

The suggestion that women over 40 who do not smoke should not take oral contraceptives is based on information from older high-dose pills and on less-selective use of pills than is practiced today. An Advisory Committee of the FDA discussed this issue in 1989 and recommended that the benefits of oral contraceptive use by healthy, non-smoking women over 40 years of age may outweigh the possible risks. However, all women, especially older women, are cautioned to use the lowest-dose pill that is effective.

WARNING SIGNALS

If any of these adverse effects occur while you are taking oral contraceptives, call your doctor immediately:

- Sharp chest pain, coughing of blood, or sudden shortness of breath (indicating a possible clot in the lung)
- Pain in the calf (indicating a possible clot in the leg)
- Crushing chest pain or heaviness in the chest (indicating a possible heart attack)
- Sudden severe headache or vomiting, dizziness or fainting, disturbances of vision or speech, weakness, or numbness in an arm or leg (indicating a possible stroke)
- Sudden partial or complete loss of vision (indicating a possible clot in the eye)
- Breast lumps (indicating possible breast cancer or fibrocystic disease of the breast; ask your doctor or healthcare provider to show you how to examine your breasts)
- Severe pain or tenderness in the stomach area (indicating a possibly ruptured liver tumor)
- Difficulty in sleeping, weakness, lack of energy, fatigue, or change in mood (possibly indicating severe depression)
- Jaundice or a yellowing of the skin or eyeballs, accompanied frequently by fever, fatigue, loss of appetite, dark-colored urine, or light-colored bowel movements (indicating possible liver problems)

SIDE EFFECTS OF ORAL CONTRACEPTIVES

1. VAGINAL BLEEDING

Irregular vaginal bleeding or spotting may occur while you are taking the pills. Irregular bleeding may vary from slight staining between menstrual periods to breakthrough bleeding, which is a flow much like a regular period. Irregular bleeding occurs most often during the first few months of oral contraceptive use, but may also occur after you have been taking the pill for some time. Such bleeding may be temporary and usually does not indicate any serious problems. It is important to continue taking your pills on schedule. If the bleeding occurs in more than one cycle or lasts for more than a few days, talk to your doctor or healthcare provider.

2. CONTACT LENSES

If you wear contact lenses and notice a change in vision or an inability to wear your lenses, contact your doctor or healthcare provider.

3. FLUID RETENTION

Oral contraceptives may cause edema (fluid retention) with swelling of the fingers or ankles and may raise your blood pressure. If you experience fluid retention, contact your doctor or healthcare provider.

4. MELASMA

A spotty darkening of the skin is possible, particularly of the face.

5. OTHER SIDE EFFECTS

Other side effects may include change in appetite, headache, nervousness, depression, dizziness, loss of scalp hair, rash, and vaginal infections.

If any of these side effects bother you, call your doctor or healthcare provider.

GENERAL PRECAUTIONS

1. Missed periods and use of oral contraceptives before or during early pregnancy.

There may be times when you may not menstruate regularly after you have completed taking a cycle of pills. If you have taken your pills regularly and miss one menstrual period, continue taking your pills for the next cycle but be sure to inform your healthcare provider before doing so. If you have not taken the pills daily as instructed and missed a menstrual period, or if you missed two consecutive menstrual periods, you may be pregnant. Check with your healthcare provider immediately to determine whether you are pregnant. Do not continue to take oral contraceptives until you are sure you are not pregnant, but continue to use another method of contraception.

There is no conclusive evidence that oral contraceptive use is associated with an increase in birth defects when taken inadvertently during early pregnancy. Previously, a few studies had reported that oral contraceptives might be associated with birth defects, but these studies have not been confirmed. Nevertheless, oral contraceptives or any other drugs should not be used during pregnancy unless clearly necessary and prescribed by your doctor. You should check with your doctor about risks to your unborn child of any medication taken during pregnancy.

2. While Breast-Feeding

If you are breast-feeding, consult your doctor before starting oral contraceptives. Some of the drug will be passed on to the child in the milk. A few adverse effects on the child have been reported, including yellowing of the skin (jaundice) and breast enlargement. In addition, oral contraceptives may decrease the amount and quality of your milk. If possible, do not use oral contraceptives while breast-feeding. You should use another method of contraception since breast-feeding provides only partial protection from becoming pregnant, and this partial protection decreases significantly as you breastfeed for longer periods of time. You should consider starting oral contraceptives only after you have weaned your child completely.

3. Laboratory Tests

If you are scheduled for any laboratory tests, tell your doctor you are taking birth-control pills. Certain blood tests may be affected by birth-control pills.

4. Drug Interactions

Certain drugs may interact with birth-control pills to make them less effective in preventing pregnancy or cause an increase in breakthrough bleeding. Such drugs include rifampin, drugs used for epilepsy such as barbiturates (for example, phenobarbital) and phenytoin (Dilantin is one brand of this drug), phenylbutazone (Butazolidin is one brand) and possibly certain antibiotics. You may need to use an additional method of contraception during any cycle in which you take drugs that can make oral contraceptives less effective.

5. Sexually transmitted diseases

This product (like all oral contraceptives) is intended to prevent pregnancy. It does not protect against transmission of HIV (AIDS) and other sexually transmitted diseases such as chlamydia, genital herpes, genital warts, gonorrhea, hepatitis B, and syphilis.

HOW TO TAKE THE PILL

IMPORTANT POINTS TO REMEMBER

BEFOREYOU START TAKING YOUR PILLS:

1. BE SURE TO READ THESE DIRECTIONS:
  Before you start taking your pills.
  Anytime you are not sure what to do.
2. THE RIGHT WAY TO TAKE THE PILL IS TO TAKE ONE PILL EVERY DAY AT THE SAME TIME.
  If you miss pills you could get pregnant. This includes starting the pack late. The more pills you miss, the more likely you are to get pregnant.
3. MANY WOMEN HAVE SPOTTING OR LIGHT BLEEDING, OR MAY FEEL SICK TO THEIR STOMACH DURING THE FIRST 1–3 PACKS OF PILLS.
  If you do feel sick to your stomach, do not stop taking the pill. The problem will usually go away. If it does not go away, check with your doctor or clinic.
4. MISSING PILLS CAN ALSO CAUSE SPOTTING OR LIGHT BLEEDING, even when you make up these missed pills.
  On the days you take two pills, to make up for missed pills, you could also feel a little sick to your stomach.
5. IF YOU HAVE VOMITING OR DIARRHEA, for any reason, or IF YOU TAKE SOME MEDICINES, including some antibiotics, your pills may not work as well.
  Use a back-up method (such as condoms, foam, or sponge) until you check with your doctor or clinic.
6. IF YOU HAVE TROUBLE REMEMBERING TO TAKE THE PILL, talk to your doctor or clinic about how to make pill-taking easier or about using another method of birth control.
7. IF YOU HAVE ANY QUESTIONS OR ARE UNSURE ABOUT THE INFORMATION IN THIS LEAFLET, call your doctor or clinic.

BEFOREYOU START TAKING YOUR PILLS

1. DECIDE WHAT TIME OF DAY YOU WANT TO TAKE YOUR PILL.
  It is important to take it at about the same time every day.
2. LOOK AT YOUR PILL PACK:
  The 28-pill pack has 21 (white) "active" pills (with hormones) to take for three weeks, followed by 1 week of reminder pills (peach) (without hormones).
3. ALSO FIND:
  - where on the pack to start taking pills,
  - in what order to take the pills (follow the arrows)
  - the week numbers as shown in picture below.
4. BE SURE YOU HAVE READY AT ALL TIMES:
  ANOTHER KIND OF BIRTH CONTROL (such as condoms, foam or sponge) to use as a back-up in case you miss pills.
  AN EXTRA, FULL PILL PACK.

WHEN TO START THE FIRSTPACK OF PILLS

You have a choice for which day to start taking your first pack of pills. Decide with your doctor or clinic which is the best day for you. Pick a time of day which will be easy to remember.

DAY 1 START:

- Pick the day label strip that starts with the first day of your period. Place this day label strip over the area that has the days of the week (starting with Sunday) pre-printed on the tablet dispenser.

Note: If the first day of your period is a Sunday, you can skip step #1.

- Take the first (white) "active" pill of the first pack during the first 24 hours of your period.
- You will not need to use a back-up method of birth control, since you are starting the pill at the beginning of your period.

SUNDAY START:

1. Take the first (white) "active" pill of the first pack on the Sunday after your period starts,even if you are still bleeding. If your period begins on Sunday, start the pack that same day.
2. Use another method of birth controlas a back-up method if you have sex anytime from the Sunday you start your first pack until the next Sunday (7 days). Condoms, foam, or the sponge are good back-up methods of birth control.

WHAT TO DO DURING THE MONTH

1. TAKE ONE PILL AT THE SAME TIME EVERY DAY UNTIL THE PACK IS EMPTY
  Do not skip pills even if you are spotting or bleeding between monthly periods or feel sick to your stomach (nausea).
  Do not skip pills even if you do not have sex very often.
2. WHEN YOU FINISH A PACK OR SWITCH YOUR BRAND OF PILLS:
  28 pills:Start the next pack on the day after your last (peach) "reminder" pill. Do not wait any days between packs.

WHAT TO DO IF YOU MISS PILLS

If you MISS 1(white) "active" pill:

1. Take it as soon as you remember. Take the next pill at your regular time. This means you may take two pills in one day.
2. You do not need to use a back-up birth control method if you have sex.

If you MISS 2(white) "active" pills in a row in WEEK 1 OR WEEK 2 of your pack:

1. Take two pills on the day you remember and two pills the next day.
2. Then take one pill a day until you finish the pack.
3. You MAY BECOME PREGNANT if you have sex in the 7 days after you miss pills. You MUST use another birth control method (such as condoms, foam, or sponge) as a back-up for those 7 days.

If you MISS 2(white) "active" pills in a row in THE 3rd WEEK:

1. If you are a Day 1 Starter:
  THROW OUT the rest of the pill pack and start a new pack that same day.
  If you are a Sunday Starter:
  Keep taking one pill every day until Sunday. On Sunday, THROW OUT the rest of the pack and start a new pack of pills that same day.
2. You may not have your period this month but this is expected.
  However, if you miss your period two months in a row, call your doctor or clinic because you might be pregnant.
3. You MAY BECOME PREGNANT if you have sex in the 7 days after you miss pills. You MUST use another birth control method (such as condoms, foam, or sponge)as a back-up for those 7 days.

If you MISS 3 OR MORE(white) "active" pills in a row (during the first 3 weeks).

1. If you are a Day 1 Starter:
  THROW OUT the rest of the pill pack and start a new pack that same day.
  If you are a Sunday Starter:
  Keep taking 1 pill every day until Sunday. On Sunday, THROW OUT the rest of the pack and start a new pack of pills that same day.
2. You may not have your period this month but this is expected. However, if you miss your period two months in a row, call your doctor or clinic because you might be pregnant.
3. You MAY BECOME PREGNANT if you have sex in the 7 days after you miss pills. You MUST use another birth control method (such as condoms, foam, or sponge) as a back-up for those 7 days.

A REMINDER FOR THOSE ON 28-DAY PACKS:

If you forget any of the 7 (peach) "reminder" pills in Week 4:

THROW AWAY the pills you missed.

Keep taking one pill each day until the pack is empty. You do not need a back-up method.

FINALLY, IF YOU ARE STILL NOT SURE WHAT TO DO ABOUT THE PILLS YOU HAVE MISSED:

Use a BACK-UP METHOD anytime you have sex.

KEEP TAKING ONE ACTIVE PILL EACH DAY until you can reach your doctor or clinic.

PREGNANCY DUE TO PILL FAILURE

The incidence of pill failure resulting in pregnancy is approximately less than 1.0% if taken every day as directed, but more typical failure rates are less than 3.0%. If failure does occur, the risk to the fetus is minimal.

PREGNANCY AFTER STOPPING THE PILL

There may be some delay in becoming pregnant after you stop using oral contraceptives, especially if you had irregular menstrual cycles before you used oral contraception. It may be advisable to postpone contraception until you begin menstruating regularly once you have stopped taking the pill and desire pregnancy.

There does not appear to be any increase in birth defects in newborn babies when pregnancy occurs soon after stopping the pill.

OVERDOSAGE

Serious ill effects have not been reported following ingestion of large doses of oral contraceptives by young children. Overdosage may cause nausea and withdrawal bleeding in females. In case of overdosage, contact your healthcare provider or pharmacist.

OTHER INFORMATION

Your healthcare provider will take a medical and family history before prescribing oral contraceptives and will examine you. The physical examination may be delayed to another time if you request it and the healthcare provider believes that it is appropriate to postpone it. You should be reexamined at least once a year. Be sure to inform your healthcare provider if there is a family history of any of the conditions listed previously in this leaflet. Be sure to keep all appointments with your healthcare provider, because this is a time to determine if there are early signs of side effects of oral contraceptive use.

Do not use the drug for any condition other than the one for which it was prescribed. This drug has been prescribed specifically for you; do not give it to others who may want birth-control pills.

HEALTH BENEFITS FROM ORAL CONTRACEPTIVES

In addition to preventing pregnancy, use of oral contraceptives may provide certain benefits. They are:

- Menstrual cycles may become more regular
- Blood flow during menstruation may be lighter and less iron may be lost. Therefore, anemia due to iron deficiency is less likely to occur.
- Pain or other symptoms during menstruation may be encountered less frequently
- Ovarian cysts may occur less frequently
- Ectopic (tubal) pregnancy may occur less frequently
- Noncancerous cysts or lumps in the breast may occur less frequently
- Acute pelvic inflammatory disease may occur less frequently
- Oral contraceptive use may provide some protection against developing two forms of cancer: cancer of the ovaries and cancer of the lining of the uterus.

If you want more information about birth-control pills, ask your doctor or pharmacist. They have a more technical leaflet called the Physician Prescribing Information which you may wish to read.

Call your doctor for medical advice about side effects. You may report side effects to Mayne Pharma at 1-844-825-8500 or to FDA at 1-800-FDA-1088.

Distributed By:
Mayne Pharma
Greenville, NC 27834

Manufactured By: Patheon, Inc.
Mississauga, Ontario L5N 7K9
CANADA

Revised: February 2022

2000014482

PRINCIPAL DISPLAY PANEL - Kit Carton

NDC 51862 -545-06

Sronyx®
Levonorgestrel and Ethinyl Estradiol
Tablets USP

28-DAY REGIMEN

This product (like all oral contraceptives) is intended to prevent
pregnancy. It does not protect against HIV infection (AIDS) and
other sexually transmitted diseases.

Rx Only

6 Blister Cards, 28 Tablets Each

mayne pharma